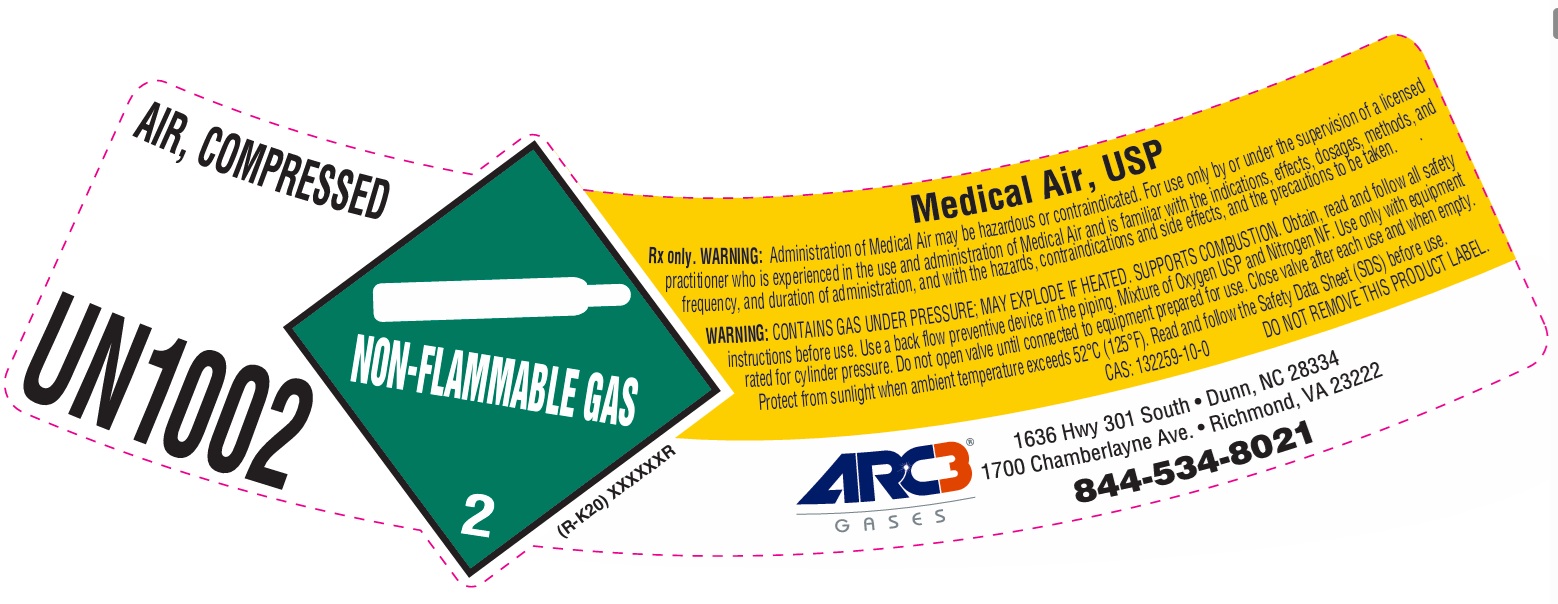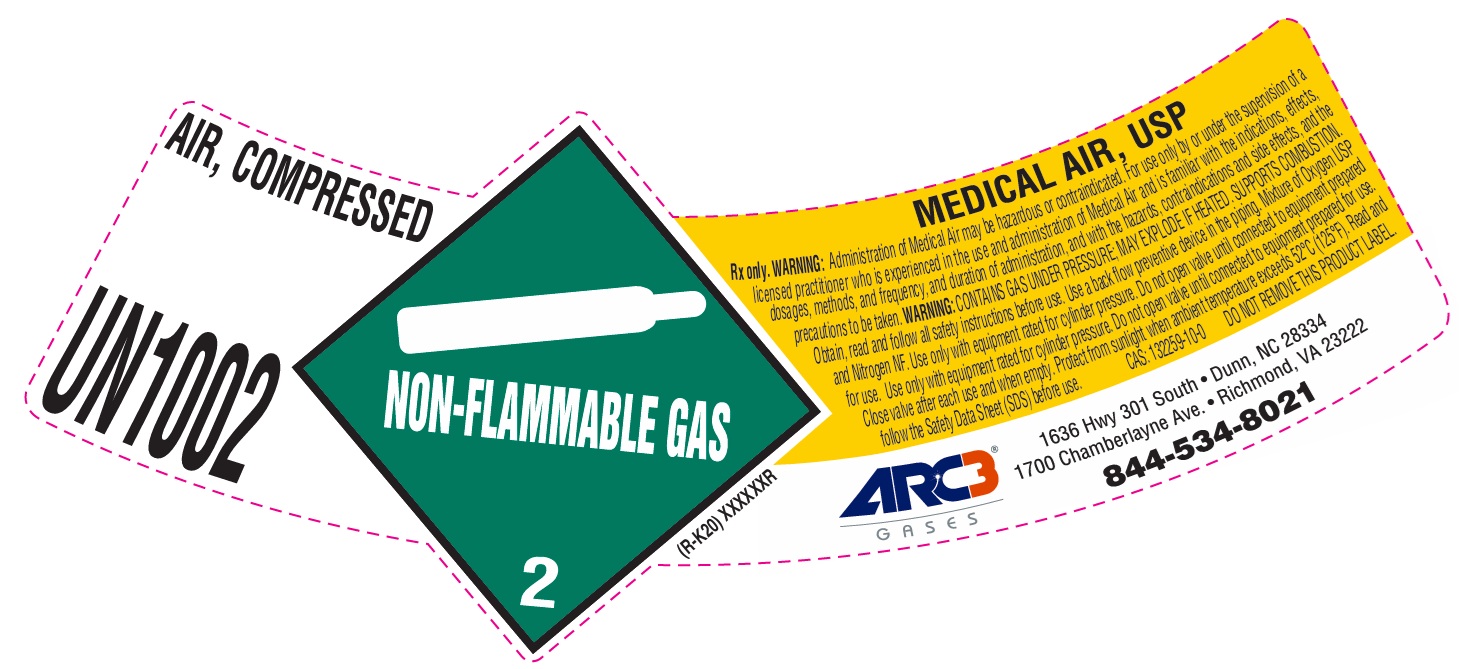 DRUG LABEL: Air
NDC: 49575-014 | Form: GAS
Manufacturer: Machine & Welding Supply Company dba Arc3 Gases South
Category: animal | Type: PRESCRIPTION ANIMAL DRUG LABEL
Date: 20251202

ACTIVE INGREDIENTS: Air 1000 mL/1 L

Medical Air Label

PACKAGE LABEL

AIR, COMPRESSED
UN1002
Medical Air, USP
Rx only. WARNING: Administration of Medical Air may be hazardous or contraindicated. For use only by or under the supervision of a licensed practitioner who is experienced in the use and administration of Medical Air and is familiar with the indications, effects, dosages, methods, and frequency, and duration of administration, and with the hazards, contraindications and side effects, and the precautions to be taken.
WARNING: CONTAINS GAS UNDER PRESSURE; MAY EXPLODE IF HEATED. SUPPORTS COMBUSTION. Obtain, read and follow all safety instructions before use. Use a back flow preventive device in the piping. Mixture of Oxygen and Nitrogen NF. Use only with equipment rated for cylinder pressure. Do not open valve until connected to equipment prepared for use. Close valve after each use and when empty. Protect from sunlight when ambient temperature exceeds 52 C (125 F). Read and follow the Safety Data Sheet (SDS) before use.
CAS: 132259-10-0 DO NOT REMOVE THIS PRODUCT LABEL.
ARC3 GASES
1636 Hwy 301 South Dunn, NC 28334
1700 Chamberlayne Ave. Richmond, VA 23222
844-534-8021

PACKAGE LABEL

AIR, COMPRESSED
UN1002
MEDICAL AIR, USP
Rx only. WARNING: Administration of Medical Air may be hazardous or contraindicated. For use only by or under the supervision of a licensed practitioner who is experienced in the use and administration of Medical Air and is familiar with the indications, effects, dosages, methods, and frequency, and duration of administration, and with the hazards, contraindications and side effects, and the precautions to be taken. WARNING: CONTAINS GAS UNDER PRESSURE; MAY EXPLODE IF HEATED. SUPPORTS COMBUSTION. Obtain, read and follow all safety instructions before use. Use a back flow preventive device in the piping. Mixture of Oxygen USP and Nitrogen NF. Use only with equipment rated for cylinder pressure. Do not open valve until connected to equipment prepared for use. Use only with equipment rated for cylinder pressure. Do not open valve until connected to equipment prepared for use. Close valve after each use and when empty. Protect from sunlight when ambient temperature exceeds 52 C (125 F). Read and follow the Safety Data Sheet (SDS) before use. CAS: 132259-10-0 DO NOT REMOVE THIS PRODUCT LABEL.
ARC3 GASES
1636 Hwy 301 South Dunn, NC 28334
1700 Chamberlayne Ave. Richmond, VA 23222
844-534-8021